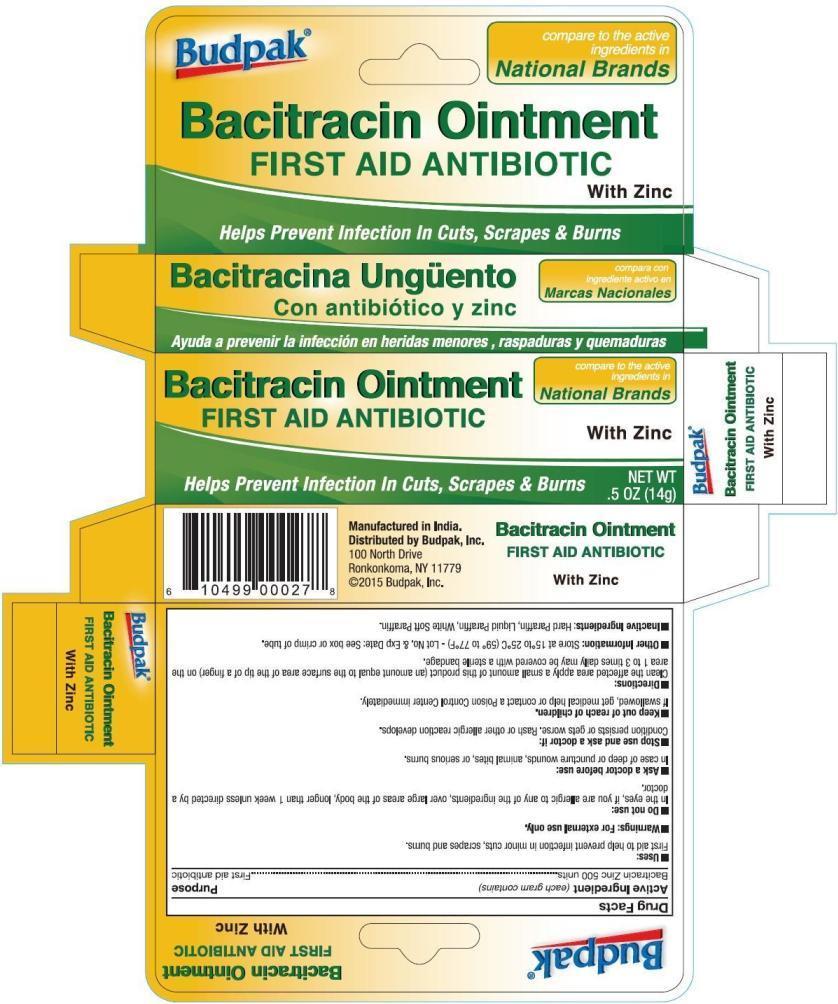 DRUG LABEL: Budpak Bacitracin
NDC: 27293-035 | Form: OINTMENT
Manufacturer: Budpak Inc.
Category: otc | Type: HUMAN OTC DRUG LABEL
Date: 20150331

ACTIVE INGREDIENTS: BACITRACIN ZINC 500 [iU]/1 g
INACTIVE INGREDIENTS: MINERAL OIL; PARAFFIN

Budpak Bacitracin Ointment

Active Ingredient (each gram contains):

Bacitracin Zinc 500 units

Purpose:

First aid antibiotic

Uses:

First aid to help prevent infection in minor cuts, scrapes, and burns.

Warnings:

For external use only.

Do not use:

In the eyes, if you are allergic to any of the ingredients, over large areas of the body, longer than 1 week unless directed by a doctor.

Ask a doctor before use:

In case of deep or puncture wounds, animal bites or serious burns

Stop use and ask a doctor if:

Condition persists or gets worse. Rash or other allergic reaction develops.

Keep out of reach of children:

If swallowed, get medical help or contact a Poison Control Center immediately.

Directions:

Clean the affected area apply a small amount of this product (an amount equal to the surface area of the tip of a finger) on the area 1 to 3 times daily may be covered with a sterile bandage.

Other Information:

Store at 15ºC to 25ºC (59ºF to 77ºF). Lot No. & Exp. Date: See box or crimp of tube.

Inactive Ingredients:

Hard Paraffin, Liquid Paraffin, White Soft Paraffin .

PACKAGE LABEL

PRINCIPAL DISPLAY PANEL

Budpak Bacitracin Ointment

First Aid Antibiotic with Zinc

NET WT .5 OZ (14 g)